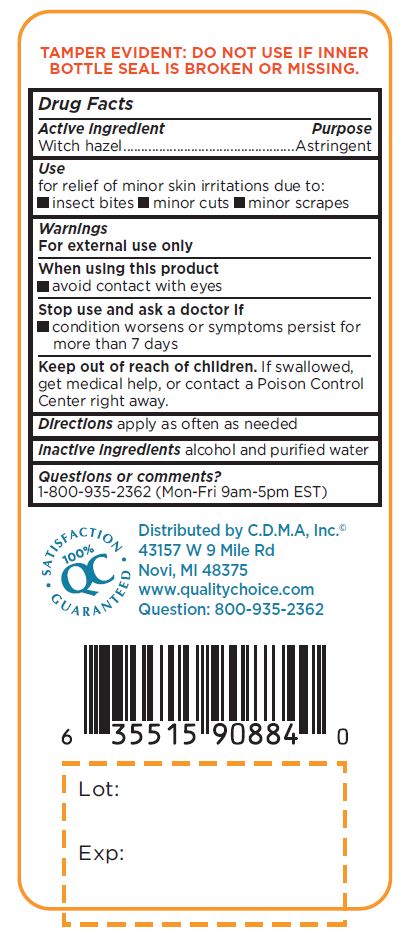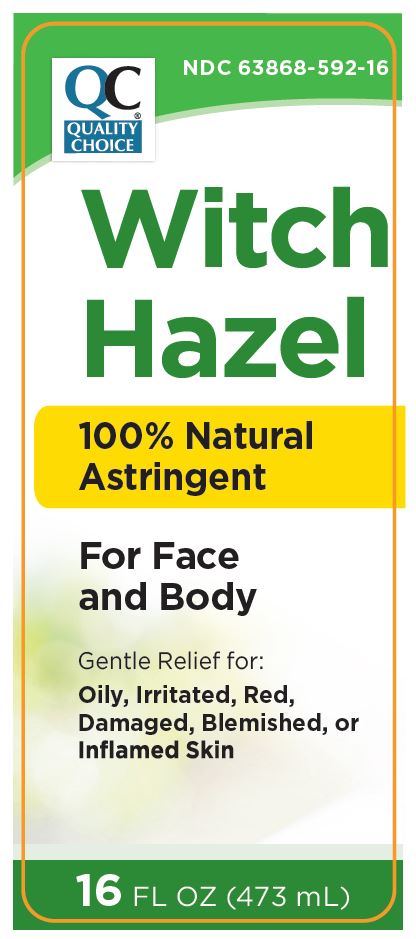 DRUG LABEL: WITCH HAZEL
NDC: 63868-592 | Form: SOLUTION
Manufacturer: CHAIN DRUG MARKETING ASSOCIATION INC
Category: otc | Type: HUMAN OTC DRUG LABEL
Date: 20241226

ACTIVE INGREDIENTS: WITCH HAZEL 85 mg/1 mL
INACTIVE INGREDIENTS: WATER; ALCOHOL

Witch Hazel
100% Natural Astringent
For Face and Body

Active Ingredient Purpose

Witch hazel ................................................Astringent

PURPOSE

Gentle Relief for:
Oily, Irritated, Red, Damaged, Blemished, or Inflamed Skin

Use

for relief of minor skin irritations due to:

- insect bites
- minor cuts
- minor scrapes

Warnings

For external use only

When using this product

- avoid contact with eyes

Stop use and ask a doctor if

- condition worsens or symptoms persist for more than 7 days

Keep out of reach of children. If swallowed, get medical help, or contact a Poison Control Center right away.

Directions

apply as often as needed

Inactive ingredients

alcohol and purified water

Questions or comments?
1-800-935-2362 (Mon-Fri 9am-5pm EST)

Distributed by C.D.M.A. lnc.
43157 W 9 Mile Rd
Novi, MI 48375
www.qualitychoice.com